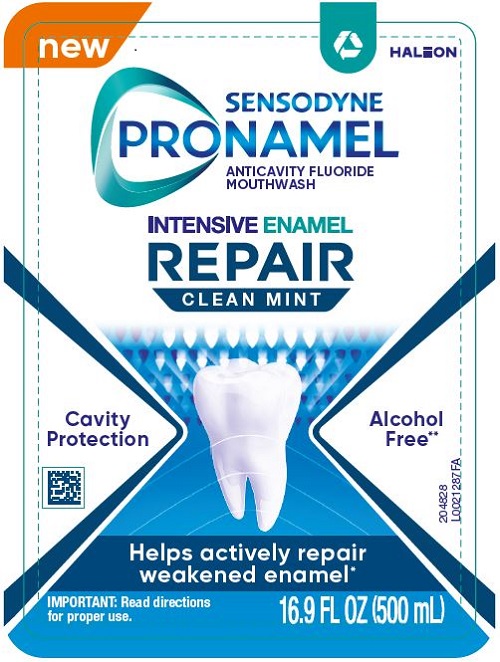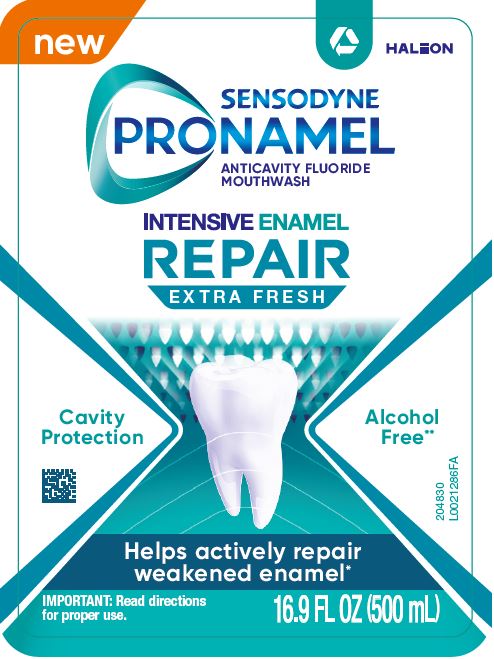 DRUG LABEL: SENSODYNE PRONAMEL
NDC: 0135-0449 | Form: LIQUID
Manufacturer: Haleon US Holdings LLC
Category: otc | Type: HUMAN OTC DRUG LABEL
Date: 20241028

ACTIVE INGREDIENTS: SODIUM FLUORIDE 0.5 mg/1 mL
INACTIVE INGREDIENTS: WATER; SORBITOL; SODIUM BENZOATE; POLOXAMER 407; BENZYL ALCOHOL; POLYSORBATE 20; PROPYLENE GLYCOL; SACCHARIN SODIUM; EDETATE DISODIUM; SODIUM PHOSPHATE, DIBASIC, ANHYDROUS; SODIUM PHOSPHATE, MONOBASIC, UNSPECIFIED FORM; EDETATE CALCIUM DISODIUM; CETYLPYRIDINIUM CHLORIDE; POTASSIUM SORBATE

Drug Facts

Active ingredient

Sodium fluoride 0.05% (0.02% w/v fluoride ion)

Purpose

Anticavity

Uses

• aids in the prevention of dental cavities.

• the combined daily use of a fluoride preventive treatment rinse and a fluoride toothpaste can help reduce the incidence of dental cavities.

Directions

• adults and children 6 years of age and older:

• use once a day after brushing your teeth with a toothpaste.
• pour 10 milliliters into cap (10 mL mark on inside of cap); do not fill above the 10 mL mark.
• vigorously swish 10 milliliters of rinse between your teeth for 1 minute and then spit out.
• do not swallow the rinse.
• do not drink from the bottle.
• do not rinse mouth with water.
• do not eat or drink for 30 minutes after rinsing.
• instruct children under 12 years of age in good rinsing habits (to minimize swallowing).
• supervise children as necessary until capable of using without supervision.

• children under 6 years of age: Consult a dentist or doctor.

Other information

• do not store above 25°C (77°F)

Inactive ingredients (Clean Mint)

water, sorbitol, sodium benzoate, poloxamer 407, benzyl alcohol, polysorbate 20, flavor, propylene glycol, sodium saccharin, disodium EDTA, disodium phosphate, monosodium phosphate, calcium disodium EDTA, cetylpyridinium chloride, potassium sorbate

Inactive ingredients (Extra Fresh)

water, sorbitol, sodium benzoate, poloxamer 407, benzyl alcohol, polysorbate 20, flavor, propylene glycol, sodium saccharin, disodium EDTA, disodium phosphate, monosodium phosphate, calcium disodium EDTA, cetylpyridinium chloride, potassium sorbate, FD&C blue no. 1

Questions or comments?

1-866-844-2797

Other Information

Re-mineralizing action for strong and protected teeth*

✓ Alcohol Free**
✓ SLS Free
✓ Paraben Free
✓ Dye Free

ALWAYS FOLLOW THE LABEL

Do not use if printed safety seal around cap is broken or missing.

*when used as directed with a fluoride toothpaste
**contains no ethanol

Distributed by: Haleon, Warren, NJ 07059
Trademarks are owned or licensed to the Haleon group of companies. ©2023 Haleon group of companies or its licensor.

Made in Taiwan

Principal Display Panel (Clean Mint)

New

SENSODYNE

PRONAMEL

ANTICAVITY FLUORIDE MOUTHWASH

INTENSIVE ENAMEL

REPAIR

CLEAN MINT

Cavity
Protection

Alcohol
Free**

Helps actively repair weakened enamel*

IMPORTANT: Read directions for proper use

16.9 FL OZ (500 mL)

Front: 204828

Back: 204832

Principal Display Panel (Extra Fresh)

New

SENSODYNE

PRONAMEL

ANTICAVITY FLUORIDE MOUTHWASH

INTENSIVE ENAMEL

REPAIR

EXTRA FRESH

Cavity
Protection

Alcohol
Free**

Helps actively repair weakened enamel*

IMPORTANT: Read directions for proper use

16.9 FL OZ (500 mL)

Front: 204830

Back: 204831